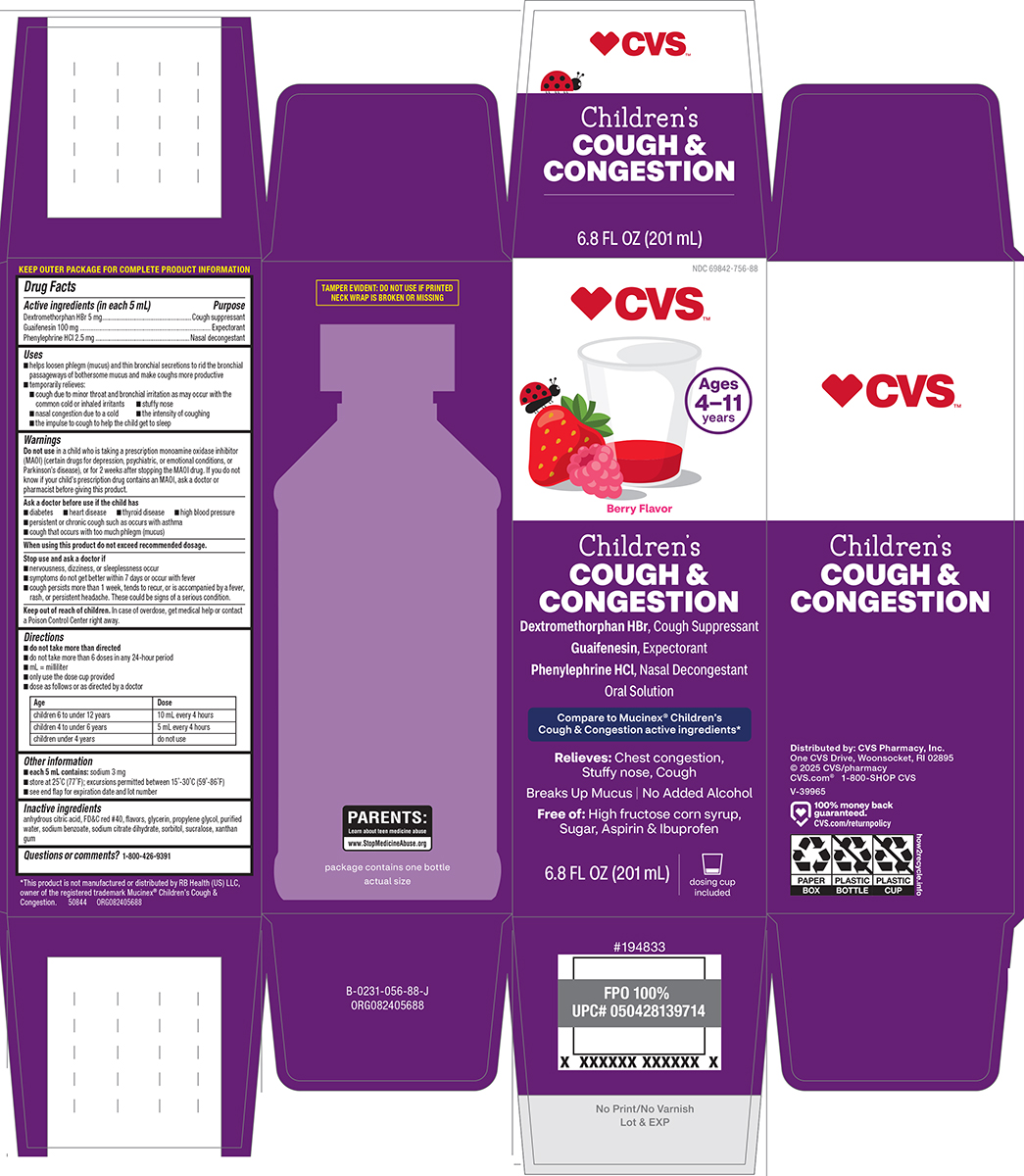 DRUG LABEL: Congestion and Cough
NDC: 69842-756 | Form: SOLUTION
Manufacturer: CVS PHARMACY
Category: otc | Type: HUMAN OTC DRUG LABEL
Date: 20260105

ACTIVE INGREDIENTS: DEXTROMETHORPHAN HYDROBROMIDE 5 mg/5 mL; GUAIFENESIN 100 mg/5 mL; PHENYLEPHRINE HYDROCHLORIDE 2.5 mg/5 mL
INACTIVE INGREDIENTS: ANHYDROUS CITRIC ACID; FD&C RED NO. 40; GLYCERIN; PROPYLENE GLYCOL; WATER; SODIUM BENZOATE; TRISODIUM CITRATE DIHYDRATE; SORBITOL; SUCRALOSE; XANTHAN GUM

CVS 44-056

Active ingredients (in each 5 mL)

Dextromethorphan HBr 5 mg
Guaifenesin 100 mg
Phenylephrine HCl 2.5 mg

Purpose

Cough suppressant
Expectorant
Nasal decongestant

Uses

- helps loosen phlegm (mucus) and thin bronchial secretions to rid the bronchial passageways of bothersome mucus and make coughs more productive
- temporarily relieves:
  - cough due to minor throat and bronchial irritation as may occur with the common cold or inhaled irritants
  - stuffy nose
  - nasal congestion due to a cold
  - the intensity of coughing
  - the impulse to cough to help the child get to sleep

Warnings

Do not use

in a child who is taking a prescription monoamine oxidase inhibitor (MAOI) (certain drugs for depression, psychiatric, or emotional conditions, or Parkinson’s disease), or for 2 weeks after stopping the MAOI drug. If you do not know if your child’s prescription drug contains an MAOI, ask a doctor or pharmacist before giving this product.

Ask a doctor before use if the child has

- diabetes
- heart disease
- thyroid disease
- high blood pressure
- persistent or chronic cough such as occurs with asthma
- cough that occurs with too much phlegm (mucus)

When using this product

do not exceed recommended dosage.

Stop use and ask a doctor if

- nervousness, dizziness, or sleeplessness occur
- symptoms do not get better within 7 days or occur with fever
- cough persists more than 1 week, tends to recur, or is accompanied by a fever, rash, or persistent headache. These could be signs of a serious condition.

Keep out of reach of children.

In case of overdose, get medical help or contact a Poison Control Center right away.

Directions

- do not take more than directed
- do not take more than 6 doses in any 24-hour period
- mL = milliliter
- only use the dose cup provided
- dose as follows or as directed by a doctor

Age | Dose
children 6 to under 12 years | 10 mL every 4 hours
children 4 to under 6 years | 5 mL every 4 hours
children under 4 years | do not use

Other information

- each 5 mL contains: sodium 3 mg
- store at 25°C (77°F); excursions permitted between 15°-30°C (59°-86°F)
- see end flap for expiration date and lot number

Inactive ingredients

anhydrous citric acid, FD&C red #40, flavors, glycerin, propylene glycol, purified water, sodium benzoate, sodium citrate dihydrate, sorbitol, sucralose, xanthan gum

Questions or comments?

1-800-426-9391

Principal Display Panel

♥CVS™

NDC 69842-756-88

Berry Flavor

Children's
Cough &
Congestion

DEXTROMETHORPHAN HBr,
Cough suppressant
GUAIFENESIN,
Expectorant
PHENYLEPHRINE HCl,
Nasal decongestant
Oral Solution

Compare to Mucinex®
Children's Cough & Congestion active ingredients*

Relieves: Chest congestion,
Stuffy nose, Cough

Breaks Up Mucus | No Added Alcohol
Free of: High fructose corn syrup,
Sugar, Aspirin & Ibuprofen

Ages 4-11 Years

Berry Flavor
Dosage cup included
Actual Bottle Size on Side Panel

6.8 FL OZ (201 mL)

TAMPER EVIDENT: DO NOT USE IF PRINTED
SAFETY SEAL UNDER CAP IS BROKEN OR MISSING

PARENTS:
Learn about teen medicine abuse
www.StopMedicineAbuse.org

*This product is not manufactured or distributed by RB Health (US) LLC,
owner of the registered trademark Mucinex® Children’s Cough &
Congestion. 50844 ORG082405688

Distributed by:
CVS Pharmacy, Inc.
One CVS Drive
Woonsocket, RI 02895
© 2025 CVS/pharmacy
CVS.com®
1-800-SHOP CVS
V-39965

100% money back
guaranteed.
CVS.com/returnpolicy

CVS 44-056